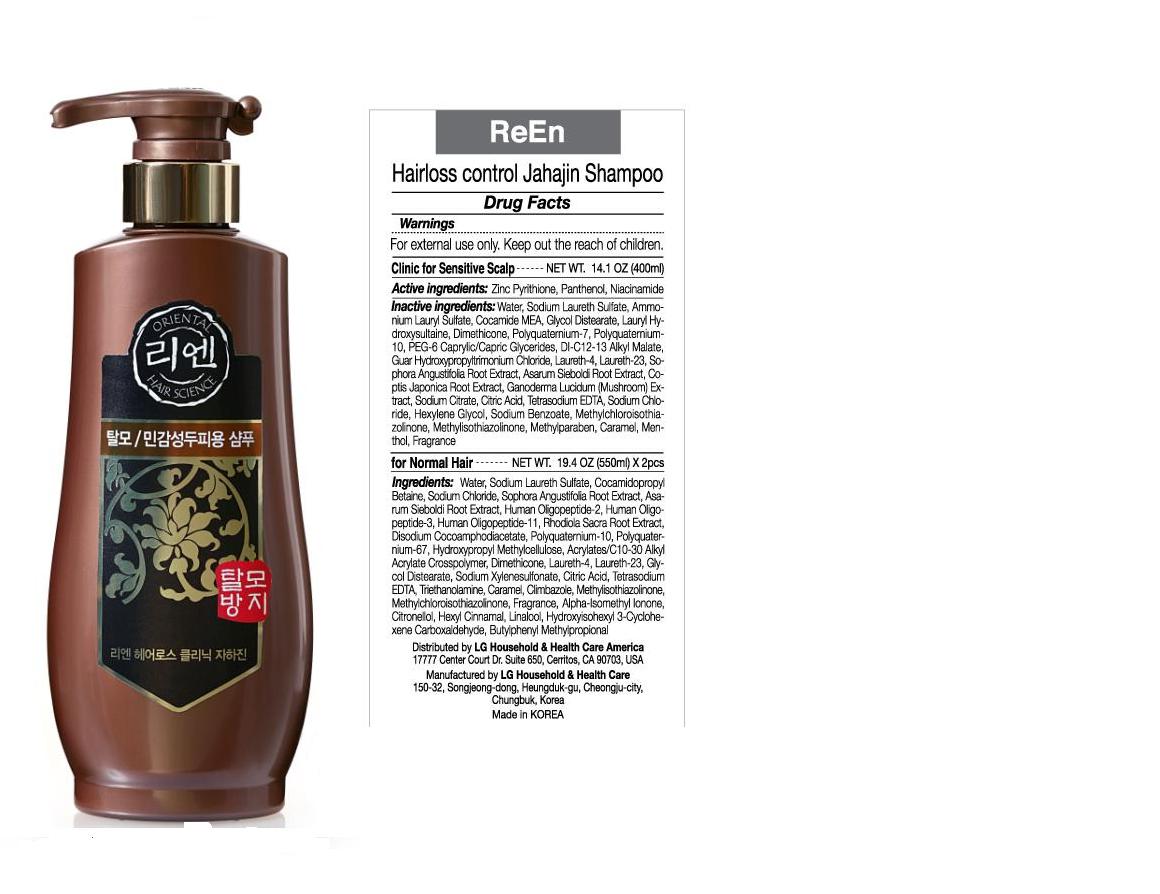 DRUG LABEL: ReEn Hairloss Clinic Jahajin Shampoo for Sensitive Scalp
NDC: 53208-516 | Form: LIQUID
Manufacturer: LG Household and Healthcare, Inc.
Category: otc | Type: HUMAN OTC DRUG LABEL
Date: 20110406

ACTIVE INGREDIENTS: PYRITHIONE ZINC 1 mL/100 mL; NIACINAMIDE 0.1 mL/100 mL; PANTHENOL 0.2 mL/100 mL
INACTIVE INGREDIENTS: Water; SODIUM LAURETH SULFATE; AMMONIUM LAURYL SULFATE; COCO MONOETHANOLAMIDE; GLYCOL DISTEARATE; DIMETHICONE; POLYQUATERNIUM-10 (400 CPS AT 2%); CHLORIDE ION; LAURETH-4; LAURETH-23; SOPHORA FLAVESCENS ROOT; ASARUM SIEBOLDII ROOT; COPTIS JAPONICA ROOT; REISHI; SODIUM CITRATE; CITRIC ACID MONOHYDRATE; EDETATE SODIUM; SODIUM CHLORIDE; HEXYLENE GLYCOL; SODIUM BENZOATE; HEXYLENE GLYCOL; SODIUM BENZOATE; METHYLCHLOROISOTHIAZOLINONE; METHYLISOTHIAZOLINONE; METHYLPARABEN; CARAMEL; MENTHOL

Drug Fact

ACTIVE INGREDIENT

PYRITHIONE ZINC 1%
PANTHENOL 0.2%
NIACINAMIDE 0.1%

WARNINGS

For external use only.

Keep out the reach of children.

INACTIVE INGREDIENT

WATER, SODIUM LAURETH SULFATE, AMMONIUM LAURYL SULFATE, COCO MONOETHANOLAMIDE, GLYCOL DISTEARATE, DIMETHICONE, POLYQUATERNIUM-10 (400 CPS AT 2%), CHLORIDE ION, LAURETH-4, LAURETH-23, SOPHORA FLAVESCENS ROOT, ASARUM SIEBOLDII ROOT, COPTIS JAPONICA ROOT, REISHI, SODIUM CITRATE, CITRIC ACID MONOHYDRATE, EDETATE SODIUM, SODIUM CHLORIDE, HEXYLENE GLYCOL, SODIUM BENZOATE, METHYLCHLOROISOTHIAZOLINONE, METHYLISOTHIAZOLINONE, METHYLPARABEN, CARAMEL, MENTHOL.

INDICATIONS AND USAGE

Hairloss control Jahajin Shampoo.

Clinic for Sensitive Scalp.

DOSAGE AND ADMINISTRATION

Hairloss Shampoo.

PURPOSE

Hairloss control Jahajin Shampoo